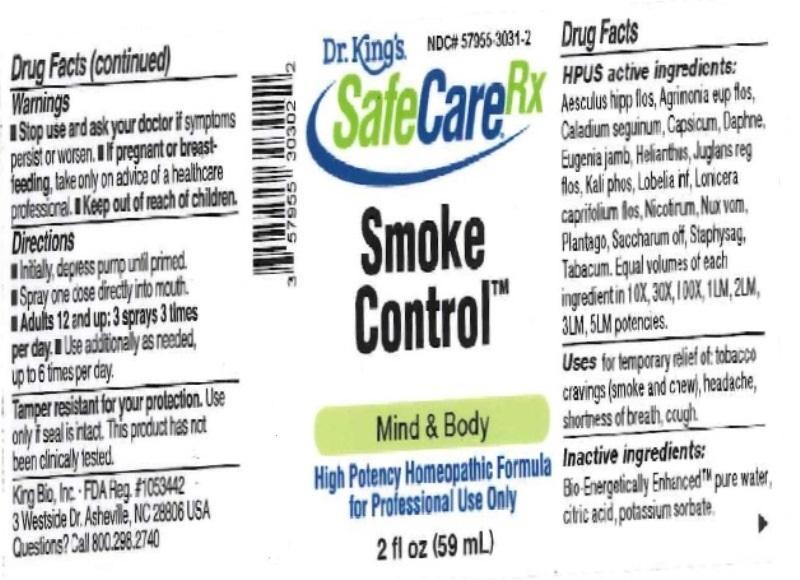 DRUG LABEL: Smoke Control
NDC: 57955-3031 | Form: LIQUID
Manufacturer: King Bio Inc.
Category: homeopathic | Type: HUMAN OTC DRUG LABEL
Date: 20161121

ACTIVE INGREDIENTS: AESCULUS HIPPOCASTANUM FLOWER 10 [hp_X]/59 mL; AGRIMONIA EUPATORIA FLOWER 10 [hp_X]/59 mL; DIEFFENBACHIA SEGUINE 10 [hp_X]/59 mL; CAPSICUM 10 [hp_X]/59 mL; DAPHNE ODORA BARK 10 [hp_X]/59 mL; SYZYGIUM JAMBOS SEED 10 [hp_X]/59 mL; HELIANTHUS ANNUUS FLOWERING TOP 10 [hp_X]/59 mL; JUGLANS REGIA FLOWERING TOP 10 [hp_X]/59 mL; POTASSIUM PHOSPHATE, DIBASIC 10 [hp_X]/59 mL; LOBELIA INFLATA 10 [hp_X]/59 mL; LONICERA CAPRIFOLIUM FLOWERING TOP 10 [hp_X]/59 mL; NICOTINE 10 [hp_X]/59 mL; STRYCHNOS NUX-VOMICA SEED 10 [hp_X]/59 mL; PLANTAGO MAJOR 10 [hp_X]/59 mL; SUCROSE 10 [hp_X]/59 mL; DELPHINIUM STAPHISAGRIA SEED 10 [hp_X]/59 mL; TOBACCO LEAF 10 [hp_X]/59 mL
INACTIVE INGREDIENTS: WATER; ANHYDROUS CITRIC ACID; POTASSIUM SORBATE

Smoke Control

Drug Facts

____________________________________________________________________________________________________________________

HPUS active ingredients: Aesculus hippocastanum, flos, Agrimonia eupatoria, flos, Caladium seguinum, Capsicum annuum, Daphne indica, Eugenia jambosa, Helianthus annuus, Juglans regia, flos, Kali phosphoricum, Lobelia inflata, Lonicera caprifolium, flos, Nicotinum, Nux vomica, Plantago major, Saccharum officinale, Staphysagria, Tabacum. Equal volumes of each ingredient in 10X, 30X, 100X, 1LM, 2LM, 3LM, 5LM potencies.

INDICATIONS AND USAGE

Uses for temporary relief of: tobacco cravings (smoke and chew), headache, shortness of breath, cough.

INACTIVE INGREDIENT

Inactive ingredients: Bio-Energetically Enhanced pure water, citric acid, potassium sorbate.

Warnings

- Stop use and ask your doctor if symptoms persist or worsen.
- If pregnant or breast-feeding, take only on advice of a healthcare professional.

- Keep out of reach of children.

Directions:

- Initially, depress pump until primed.
- Spray one dose directly into mouth.
- Adults 12 and up: 3 sprays 3 times per day.
- Use additionally as needed, up to 6 times per day.

OTHER SAFETY INFORMATION

Tamper resistant for your protection. Use only if safety seal is intact. This product has not been clinically tested.

PURPOSE

Uses for temporary relief of:

- tobacco cravings (smoke and chew)
- headache
- shortness of breath
- cough